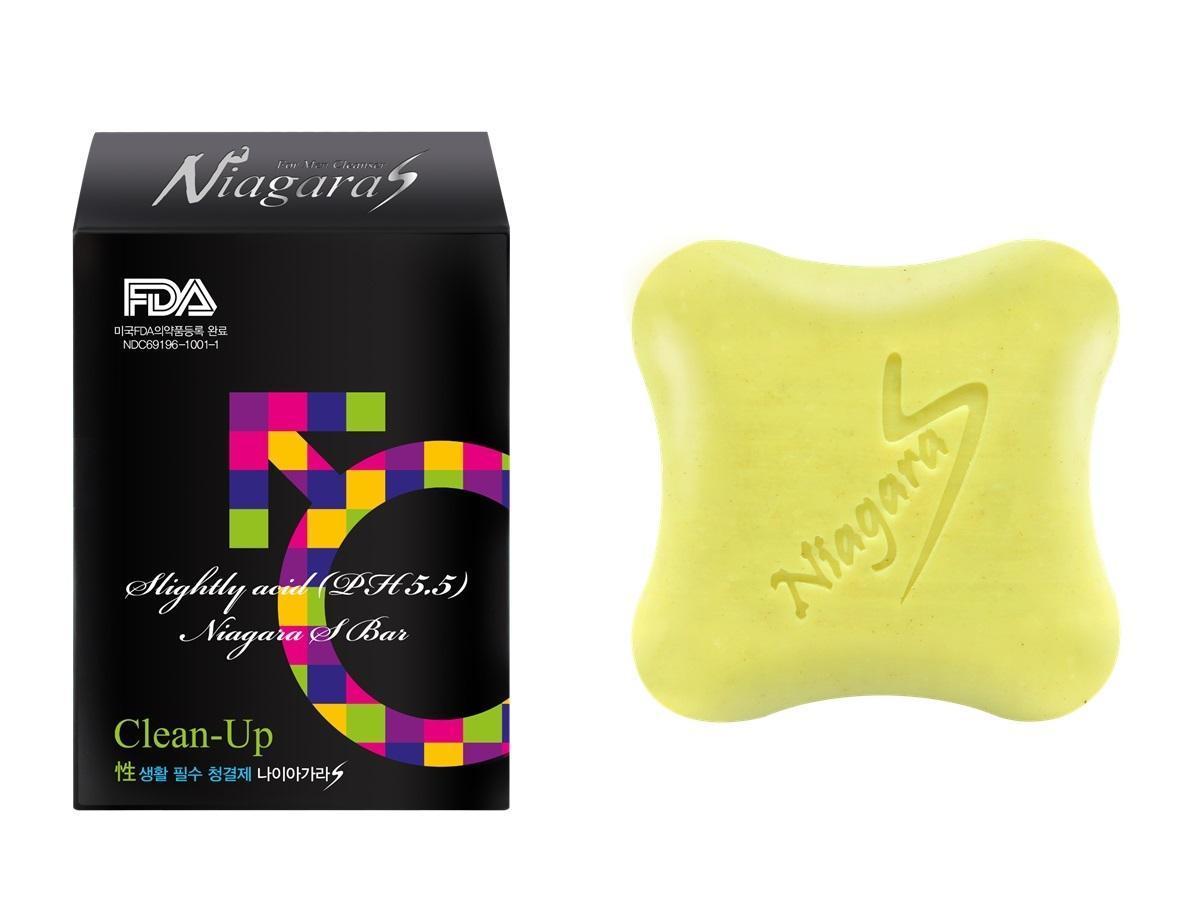 DRUG LABEL: Niagara S
NDC: 69196-1001 | Form: SOAP
Manufacturer: Sungwon Cosmetics
Category: otc | Type: HUMAN OTC DRUG LABEL
Date: 20230131

ACTIVE INGREDIENTS: GLYCERIN 1 g/100 g
INACTIVE INGREDIENTS: GINKGO; ALOE; MENTHOL

Niagara S 69196-1001-1

ACTIVE INGREDIENT

glycerin

INACTIVE INGREDIENT

palm oil, ginkgo leaf ext, aloe ext, menthol, jojoba oil, zeolite, red ginseng ext, pine ext, orange oil etc

PURPOSE

strengthen blood circulation function
deodorant
anti-microbial
strengthen sexual function

keep out of reach of the children

INDICATIONS AND USAGE

Foaming using a shower towel
Massage evenly to the 10cm above the knee to 50cm below the navel using the foaming shower towel
Furl in the important part by the shower towel and wait for about 2~3 minutes with giving strength to the hip repeating tightening and loosening 10 ~ 15 seconds
wash out with cool water

WARNINGS

do not swallow

DOSAGE AND ADMINISTRATION

for topical use only